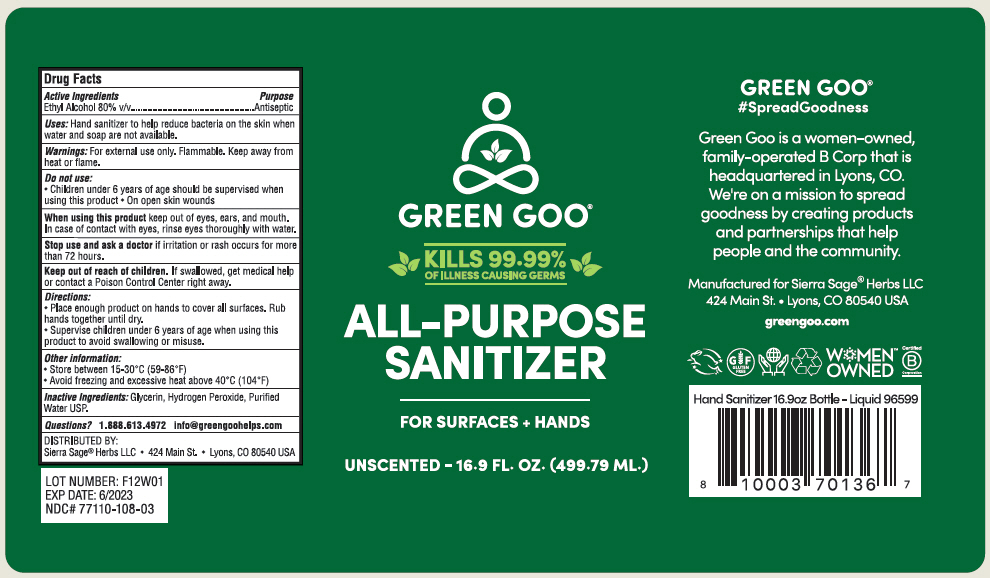 DRUG LABEL: ALL-PURPOSE SANITIZER
NDC: 77110-108 | Form: LIQUID
Manufacturer: Biominerales Pharma
Category: otc | Type: HUMAN OTC DRUG LABEL
Date: 20200811

ACTIVE INGREDIENTS: Alcohol 80 mL/100 mL
INACTIVE INGREDIENTS: GLYCERIN; HYDROGEN PEROXIDE; WATER

ALL-PURPOSE SANITIZER

Drug Facts

Active Ingredients

Ethyl Alcohol 80% v/v

Purpose

Antiseptic

Uses

Hand sanitizer to help reduce bacteria on the skin when water and soap are not available.

Warnings

For external use only. Flammable. Keep away from heat or flame.

Do not use

- Children under 6 years of age should be supervised when using this product
- On open skin wounds

When using this product keep out of eyes, ears, and mouth. In case of contact with eyes, rinse eyes thoroughly with water.

Stop use and ask a doctor if irritation or rash occurs for more than 72 hours.

Keep out of reach of children. If swallowed, get medical help or contact a Poison Control Center right away.

Directions

- Place enough product on hands to cover all surfaces. Rub hands together until dry.
- Supervise children under 6 years of age when using this product to avoid swallowing or misuse.

Other information

- Store between 15-30°C (59-86°F)
- Avoid freezing and excessive heat above 40°C (104°F)

Inactive Ingredients

Glycerin, Hydrogen Peroxide, Purified Water USP.

Questions?

1.888.613.4972 info@greengoohelps.com

DISTRIBUTED BY:
Sierra Sage® Herbs LLC • 424 Main St. • Lyons, CO 80540 USA

PRINCIPAL DISPLAY PANEL - 499.79 ML Bottle Label

GREEN GOO®

KILLS 99.99%
OF ILLNESS CAUSING GERMS

ALL-PURPOSE
SANITIZER

FOR SURFACES + HANDS

UNSCENTED - 16.9 FL. OZ. (499.79 ML.)